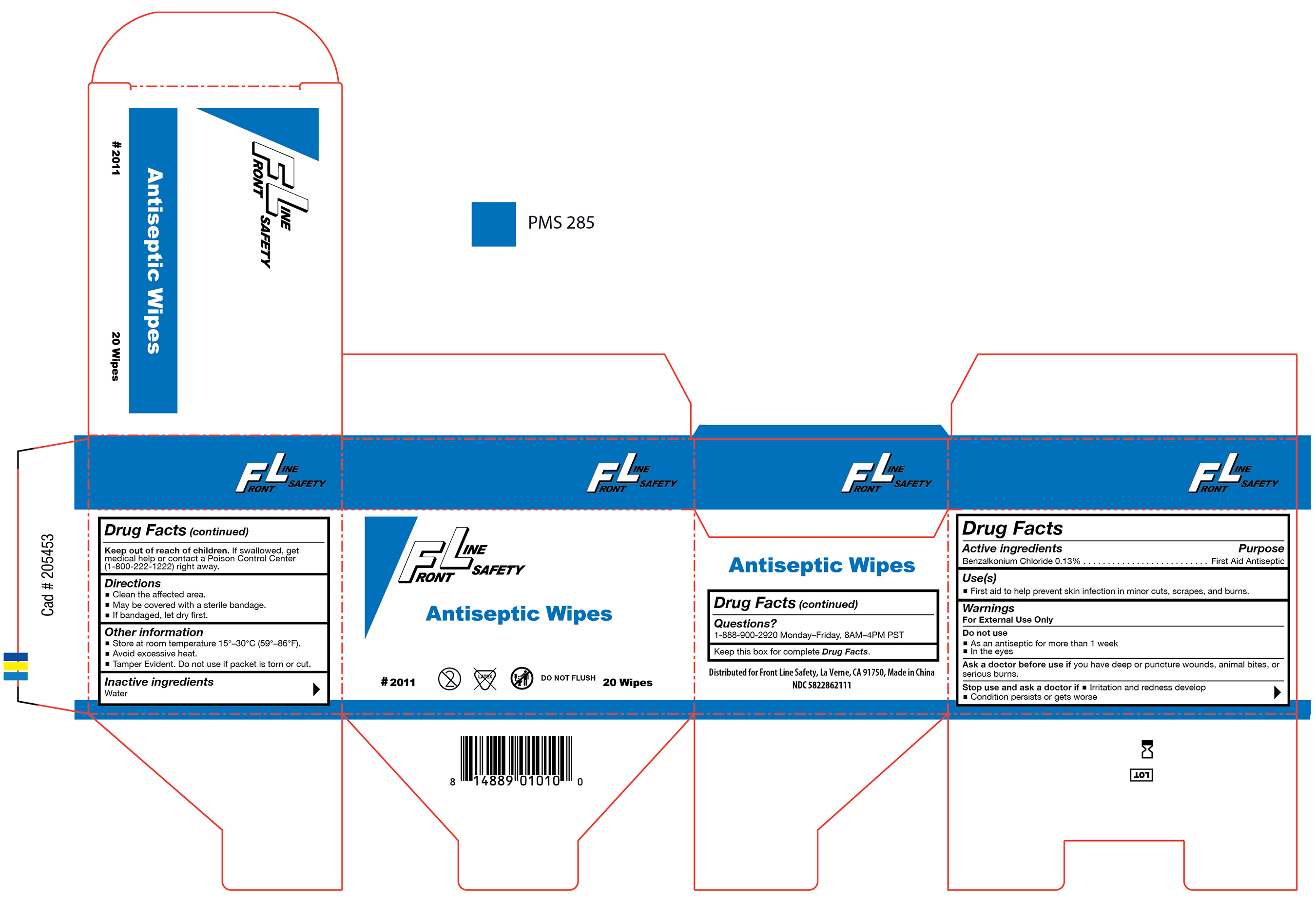 DRUG LABEL: Antiseptic Wipes
NDC: 58228-6211 | Form: SWAB
Manufacturer: Front Line Safety
Category: otc | Type: HUMAN OTC DRUG LABEL
Date: 20251215

ACTIVE INGREDIENTS: BENZALKONIUM CHLORIDE 1.3 mg/1 mL
INACTIVE INGREDIENTS: WATER

FL-2011

Active ingredient

Benzalkonium Chloride 0.13%

Purpose

First Aid Antiseptic

Use(s)

• First aid to prevent infection in minor cuts, scrapes, and burns.

Warnings

For External Use Only

Do not use

• As an antiseptic for more than 1 week

• In the eyes

Ask a doctor before use if

you have deep or puncture wounds, animal bites, or serious burns.

Stop use and ask a doctor if

• Irritation and redness develop

• Condition persists or get worse

Keep out of reach of children

If swallowed, get medical help or contact a Poison Control Center (1-800-222-1222) right away.

Directions

• Clean the affected area.

• May be covered with a sterile bandage.

• If bandaged, let dry first.

Other information

• Store at room temperature 15º-30ºC (59º-86°F).

• Avoid excessive heat.

•Tamper Evident. Do not use if packet is torn or cut.

Inactive ingredients

Water

Questions?

1-888-900-2920 Monday-Friday, 8AM-4PM PST

Label

FL-2011